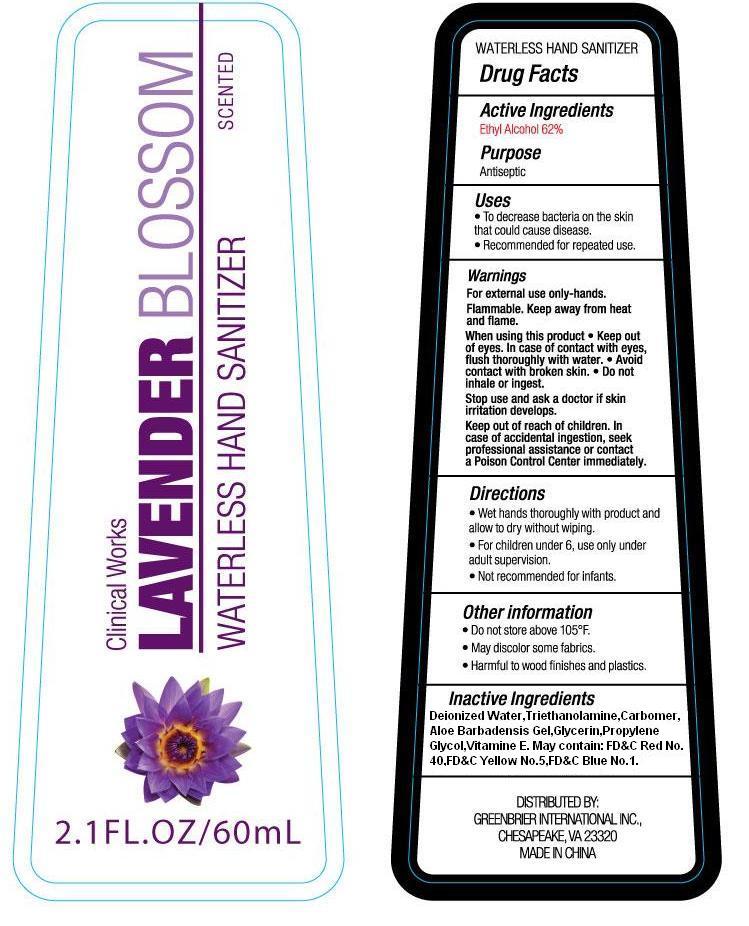 DRUG LABEL: Clinical Works  Lavender Blossom Waterless Hand Sanitizer
NDC: 50593-006 | Form: LIQUID
Manufacturer: Taizhou Xinzhixuan Daily-Use Co., Ltd.
Category: otc | Type: HUMAN OTC DRUG LABEL
Date: 20100605

ACTIVE INGREDIENTS: ALCOHOL 62.000 g/100 g
INACTIVE INGREDIENTS: WATER 35.39999 g/100 g; GLYCERIN 1.0 g/100 g; TROLAMINE 0.25 g/100 g; CARBOMER 934 0.25 g/100 g; DMDM HYDANTOIN 0.4 g/100 g; POLYOXYL 40 CASTOR OIL 0.5 g/100 g; FD&C YELLOW NO. 5 0.000003 g/100 g; FD&C BLUE NO. 1 0.000003 g/100 g; FD&C RED NO. 40 0.000004 g/100 g; LAVENDER 0.2 g/100 g

Drug Fact

Active Ingredients
Ethyl Alcohol 62%
Purpose
Antisepic

Uses

- To decrease bacteria on the skin that could cause disease.
- Recommended for repeated use

Warnings
For external use only-hands.
Flammable. Keep away from heat and flame.
When using this product, Keep out of eyes. In case of contact with eyes, flush thoroughly with water. Avoid contact with broken skin. Do not inhale or ingest.
Stop use and ask a doctor if skin irritation develops.
Keep out of reach of children. In case of accidental ingestion, seek professional assistance or contact a Poison Control Center immediately.

Directions
Wet hands thoroughly with product and allow to dry without wiping.
For children under 6,use only under adult supervision.
Not recommended for infants.

Other Information
Do not store above 105F
May discolor some fabrics.
Harmful to wood finishes and plastics

Inactive Ingredients

water(Aqua), Glycerin, Triethanolamine, Carbomer, Fragrance(parfum), PEG-40 Hydrogenated Castor Oil, DMDM Hydantoin, FD and C Yellow No. 5, FD and C Blue No. 1, FD and C Red No. 40

PACKAGE LABEL

labe